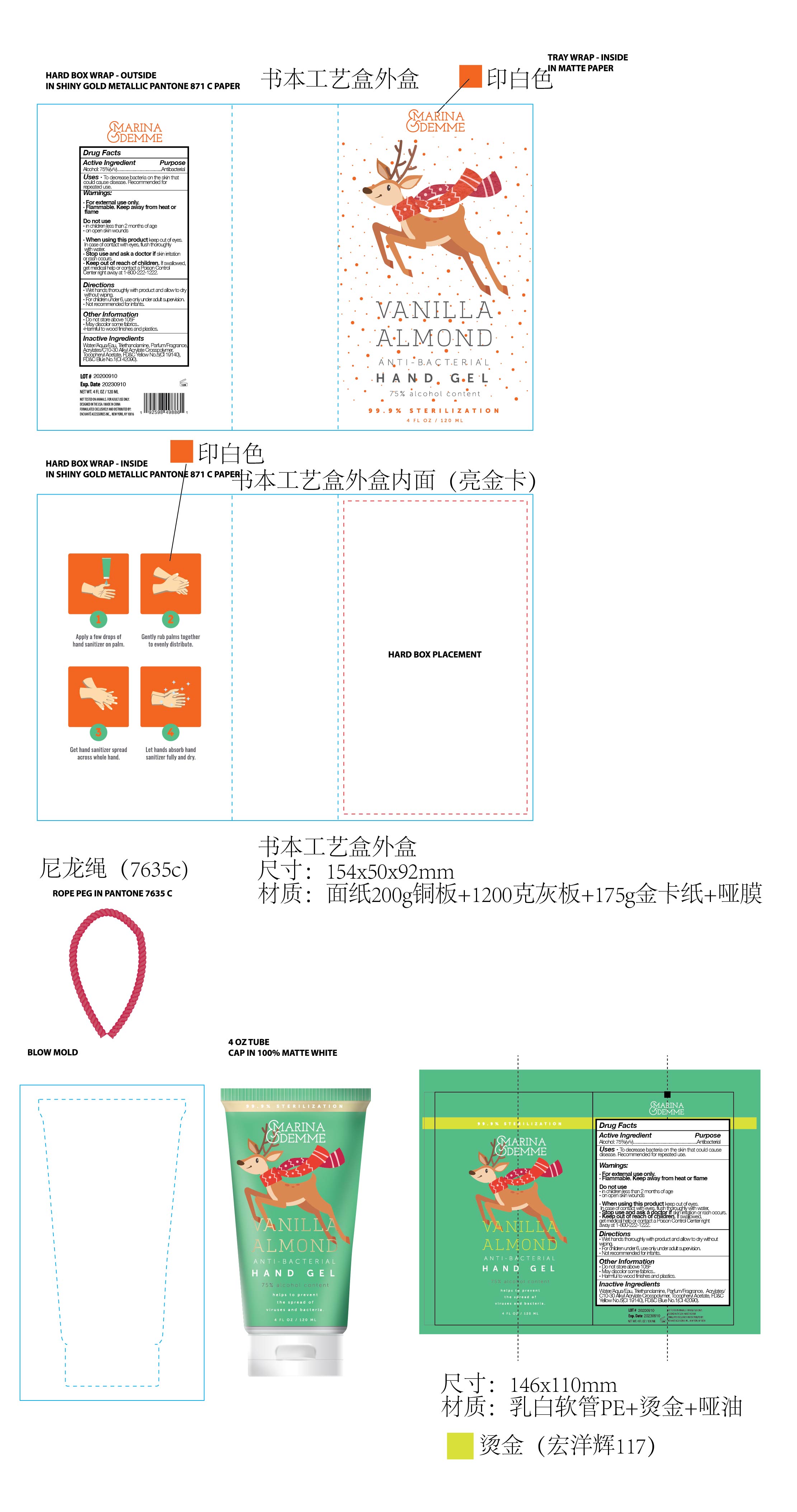 DRUG LABEL: MARINA DEMME VANILLA ALMOND ANTIBACTERIAL HAND
NDC: 50563-247 | Form: GEL
Manufacturer: ENCHANTE ACCESSORIES INC.
Category: otc | Type: HUMAN OTC DRUG LABEL
Date: 20200926

ACTIVE INGREDIENTS: ALCOHOL 75 mL/100 mL
INACTIVE INGREDIENTS: TROLAMINE; .ALPHA.-TOCOPHEROL ACETATE; FD&C BLUE NO. 1; FD&C YELLOW NO. 5; WATER

50563-247/ RX0ABST2

Active Ingredient

Ethyl Alcohol: 75% (v/v)

Purpose

Antibacterial

Use

■ To decrease bacteria on the skin that could cause disease
■Recommended for repeated use

WARNINGS

For external use only, Hands

Flammable. Keep away from heat and flame

Do not use

in children less than two months of age

on open skin wounds

When using this product, keep out of eyes.
In case of contact with eyes, flush thoroughly with water

Stop Use

Stop use and ask a doctor if skin irritation or rash occurs

keep out of reach of children

Use under adult supervision. If swallowed, get medical help or contact a poison control center right away at 1-800-222-1222

Directions

Wet hands thoroughly with product and allow to dry without wiping

For children under 6, use only under adult supervision

Not recommended for infants

Other information

Do not store above 105F

May discolor some fabrics

Harmful to wood finishes and plastics

Inactive ingredients

Water, Triehtanolamine, Parfum/Fragrance, Acrylates/C10-30 Alkyl Acrylate Crosspolymer, Tocopheryl Acetate, FD&C Yellow No.5(CI 19140), FD&C Blue No.1(CI 42090)